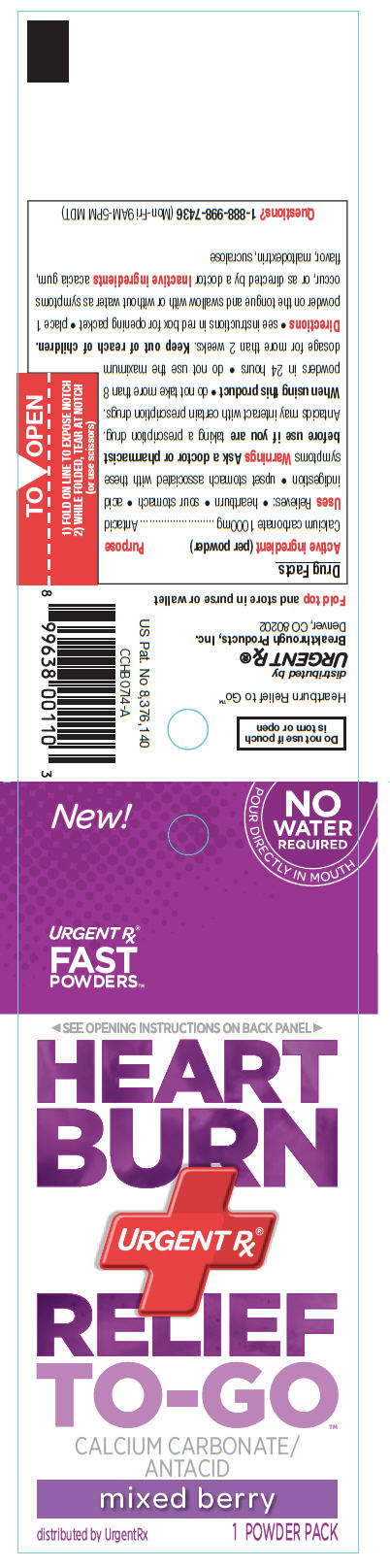 DRUG LABEL: Heartburn Relief to Go
NDC: 51596-005 | Form: POWDER
Manufacturer: Breakthrough Products Inc.
Category: otc | Type: HUMAN OTC DRUG LABEL
Date: 20141006

ACTIVE INGREDIENTS: Calcium carbonate 1000 mg/1 1
INACTIVE INGREDIENTS: acacia; maltodextrin; sucralose

Heartburn Relief to Go™

Drug Facts

Active ingredient (per powder)

Calcium carbonate 1000mg

Purpose

Antacid

Uses

Relieves:

- heartburn
- sour stomach
- acid indigestion
- upset stomach associated with these symptoms

Warnings

Ask a doctor or pharmacist before use if you are taking a prescription drug. Antacids may interact with certain prescription drugs.

When using this product

- do not take more than 8 powders in 24 hours
- do not use the maximum dosage for more than 2 weeks.

Keep out of reach of children.

Directions

- see instructions in red box for opening packet
- place 1 powder on the tongue and swallow with or without water as symptoms occur, or as directed by a doctor

Inactive ingredients

acacia gum, flavor, maltodextrin, sucralose

Questions?

1-888-998-7436 (Mon-Fri 9AM-5PM MDT)

Do not use if pouch
is torn or open

distributed by
Urgent Rx®
Breakthrough Products, Inc.
Denver, CO 80202

PRINCIPAL DISPLAY PANEL - 1 Powder Packet

NO
WATER
REQUIRED
POUR DIRECTLY IN MOUTH

New!

URGENT Rx®
FAST
POWDERS™

◀ SEE OPENING INSTRUCTIONS ON BACK PANEL ▶

HEART
BURN
URGENT Rx®
RELIEF
TO-GO™

CALCIUM CARBONATE/
ANTACID

mixed berry

distributed by UrgentRx

1 POWDER PACK